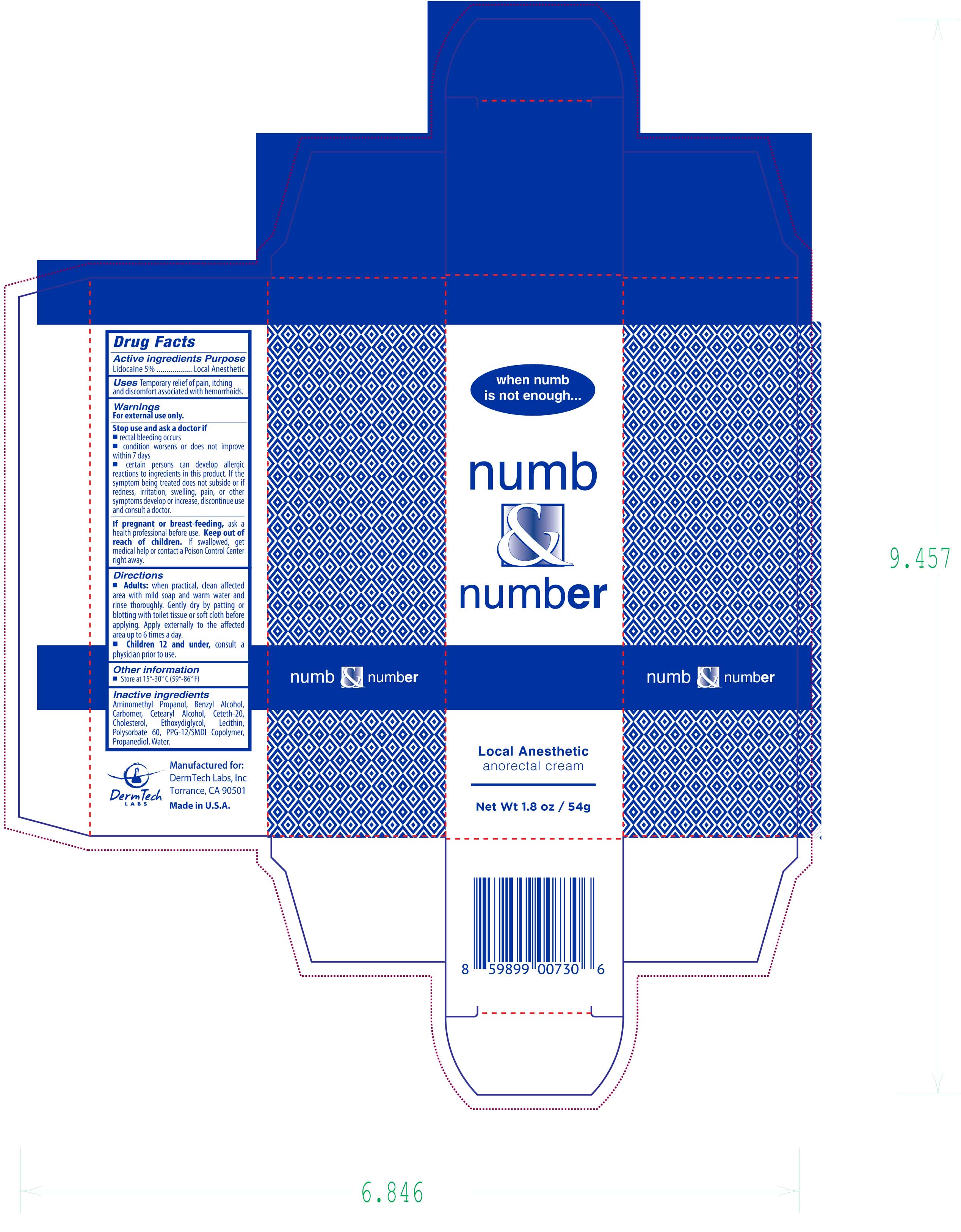 DRUG LABEL: Numb and Number Anorectal Cream
NDC: 68848-002 | Form: CREAM
Manufacturer: Dermtech Labs, Inc
Category: otc | Type: HUMAN OTC DRUG LABEL
Date: 20250326

ACTIVE INGREDIENTS: LIDOCAINE 5 g/100 g
INACTIVE INGREDIENTS: WATER; CETEARYL ALCOHOL; CETETH-20; CHOLESTEROL; PROPANEDIOL; CARBOMER; LECITHIN, SOYBEAN; PPG-12/SMDI COPOLYMER; BENZYL ALCOHOL; AMINOMETHYL PROPANOL; ETHOXYDIGLYCOL; POLYSORBATE 60

Numb and Number Anorectal Cream

Active ingredients Purpose

Lidocaine 5% .........Local Anesthetic

PURPOSE

Uses Temporary relief of pain, itching and discomfort associated with hemmrroids

Keep out of reach of children. If swallowed, get medical help or contact a Poison Control Center right away.

Stop use and ask a doctor if

- rectal bleeding occurs
- condition worsens or does not improve within 7 days
- certain persons can develop allergic reactions to ingredients in this product. If the symptom being treated does not subside or if redness, irritation, swelling, pain, or other symptoms develop or increase, discontinue use and consult a doctor.

Warnings

For external use only.

If pregnant or breast-feeding, ask a health professional before use.

Directions

- Adults: when practical, clean affected area with mild soap and warm water and rinse thoroughly. Gently dry by patting or blotting with toilet tissue or soft cloth before applying. Apply externally to the affected area up to 6 times a day.
- Children 12 and under, consult a physician prior to use.

Inactive Ingredients

Aminomethyl Propanol, Benzyl Alcohol, Carbomer, Cetearyl Alcohol, Ceteth-20, Cholesterol, Ethoxydiglycol, Lecithin, Polysorbate 60, PPG-12/SMDI Copolymer, Propanediol, Water.

PACKAGE LABEL

numb & number

Local Anesthetic

anorectal cream

Net Wt 1.8 oz / 54g